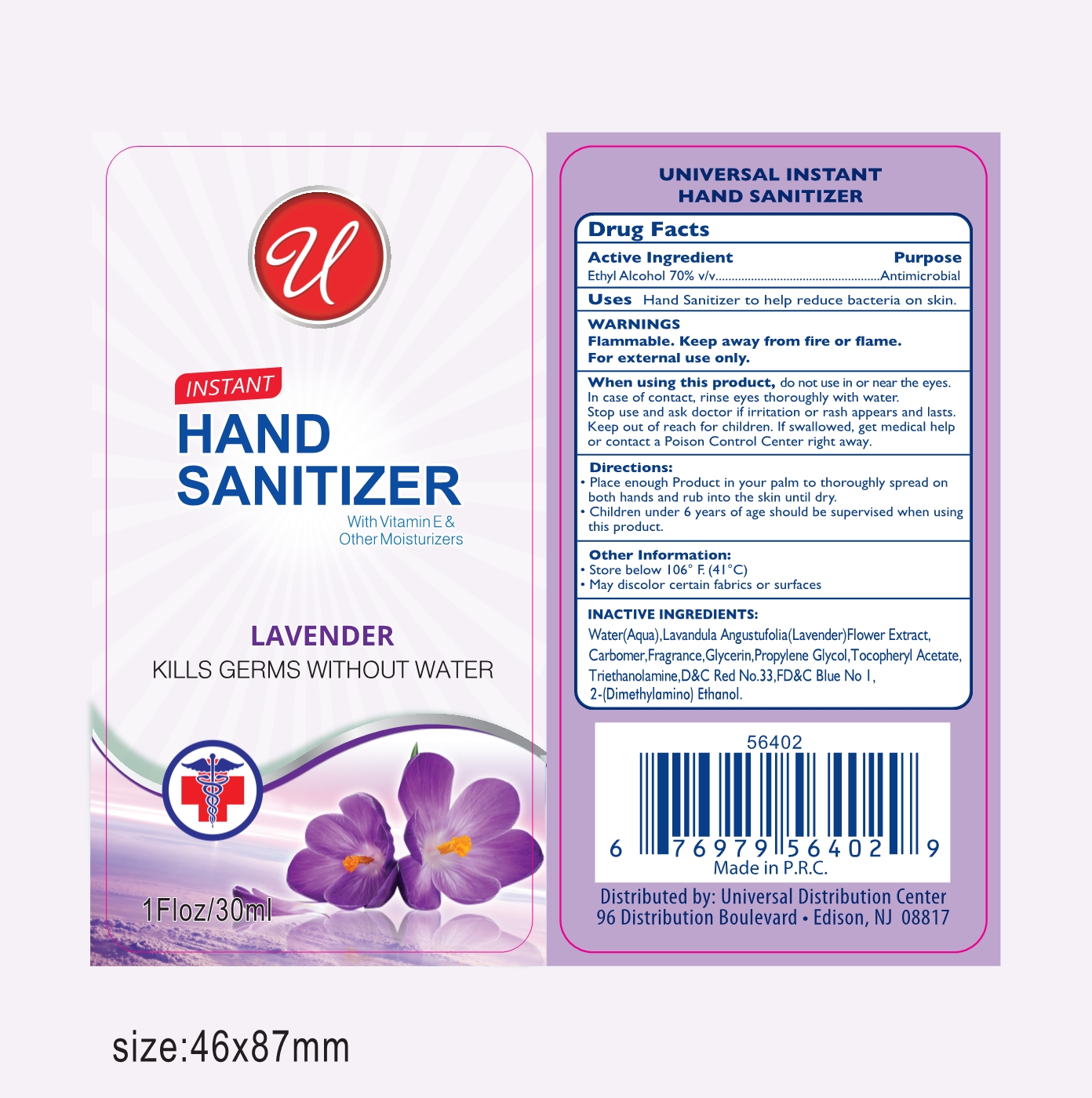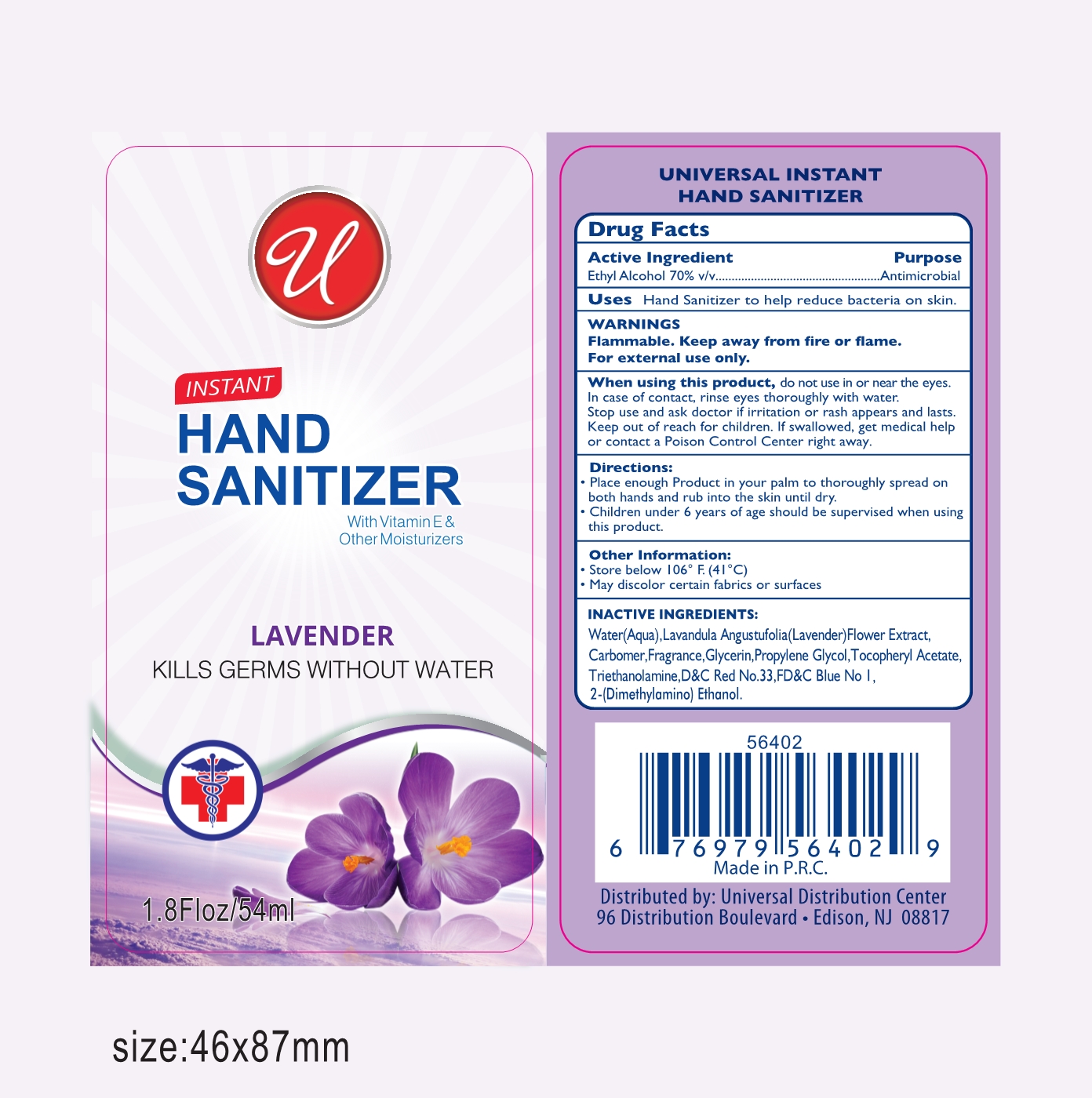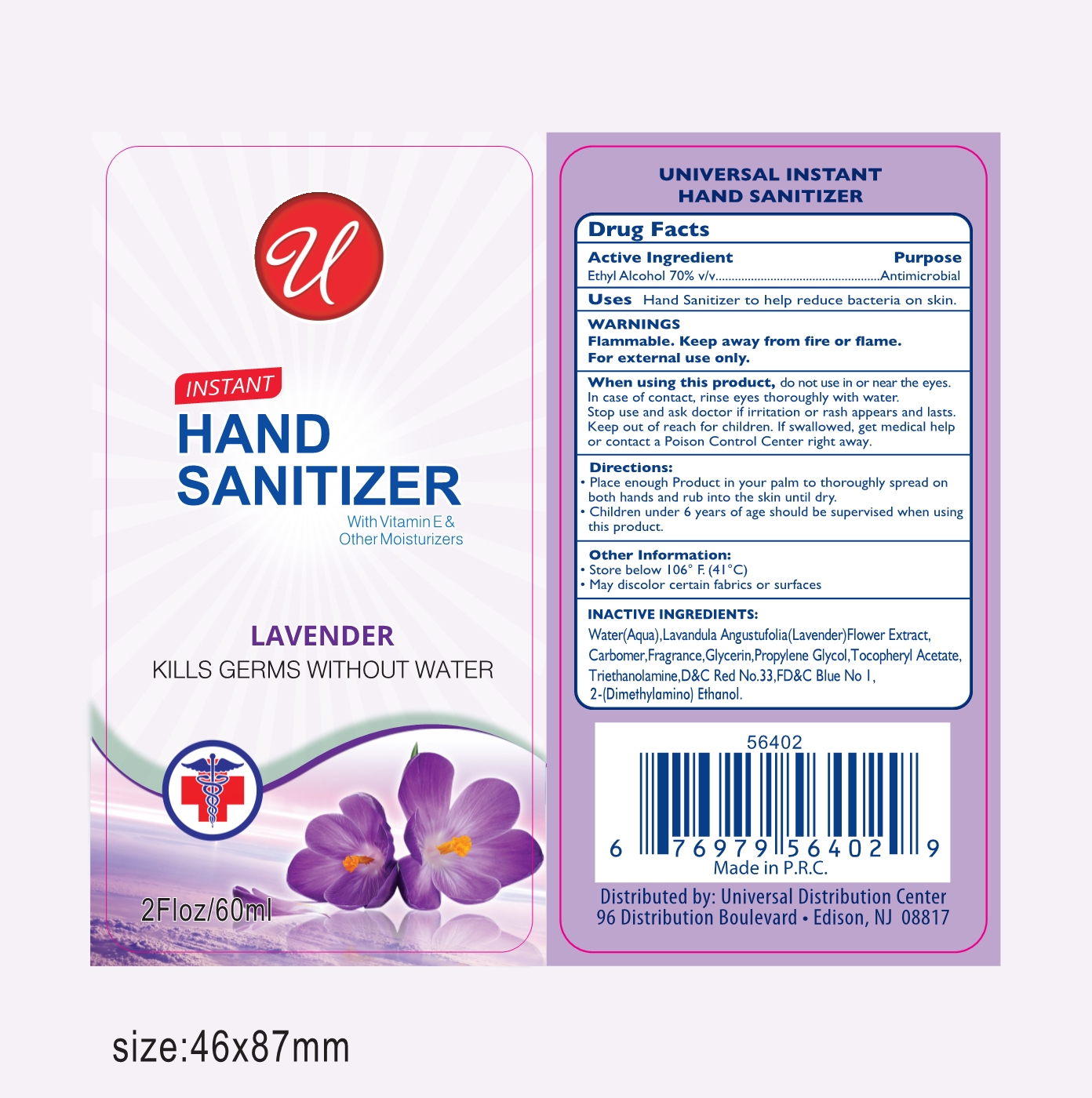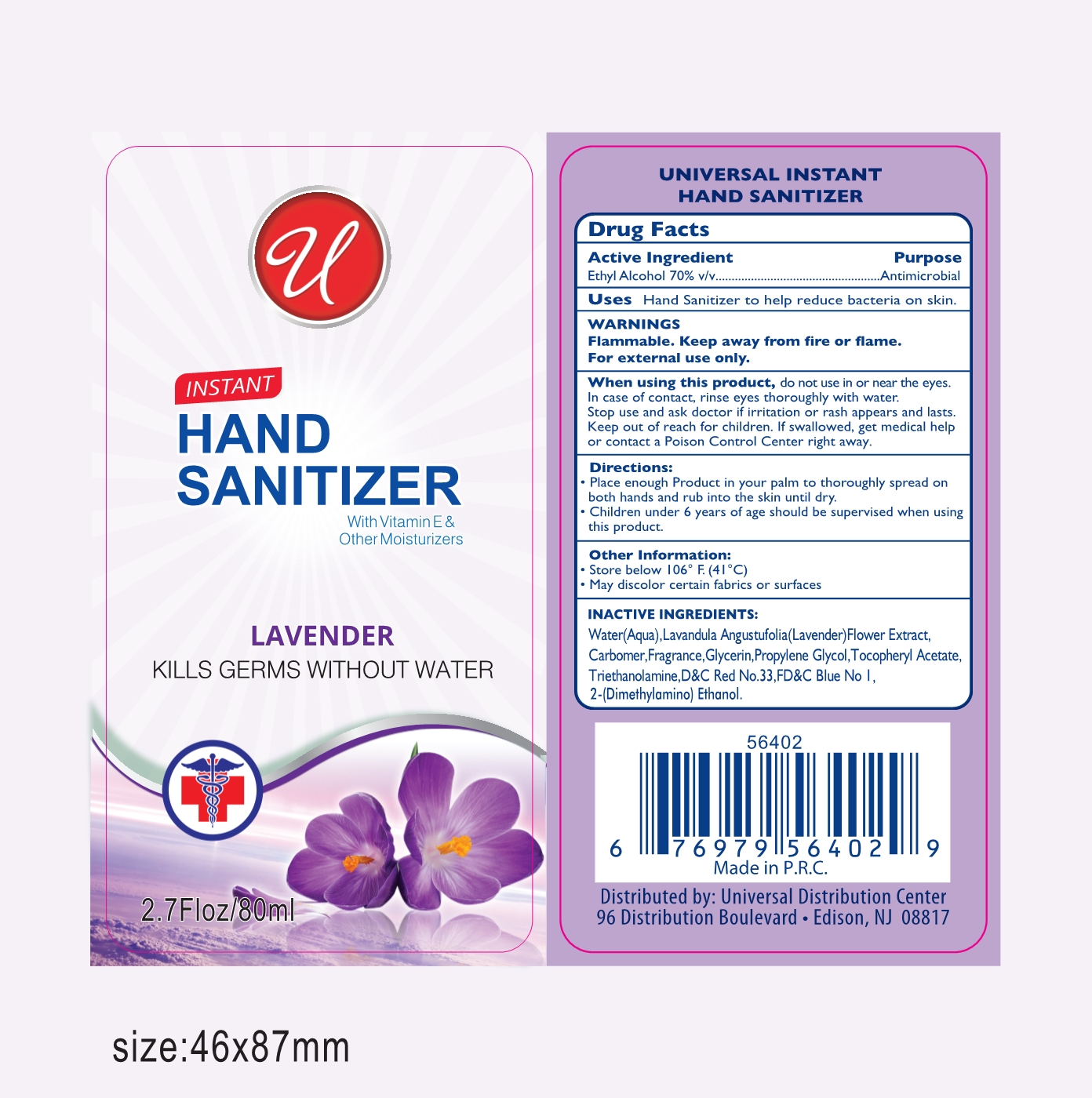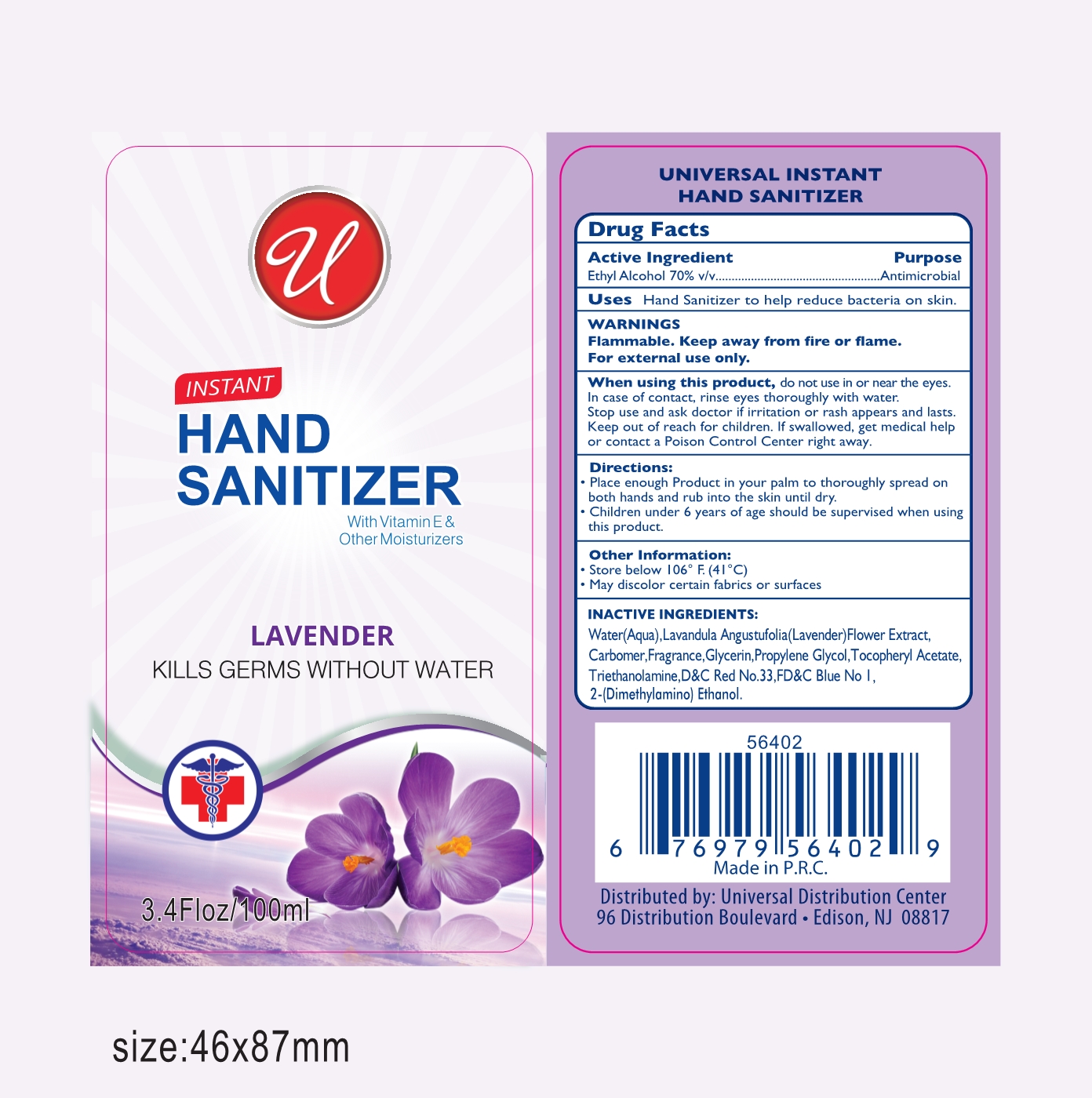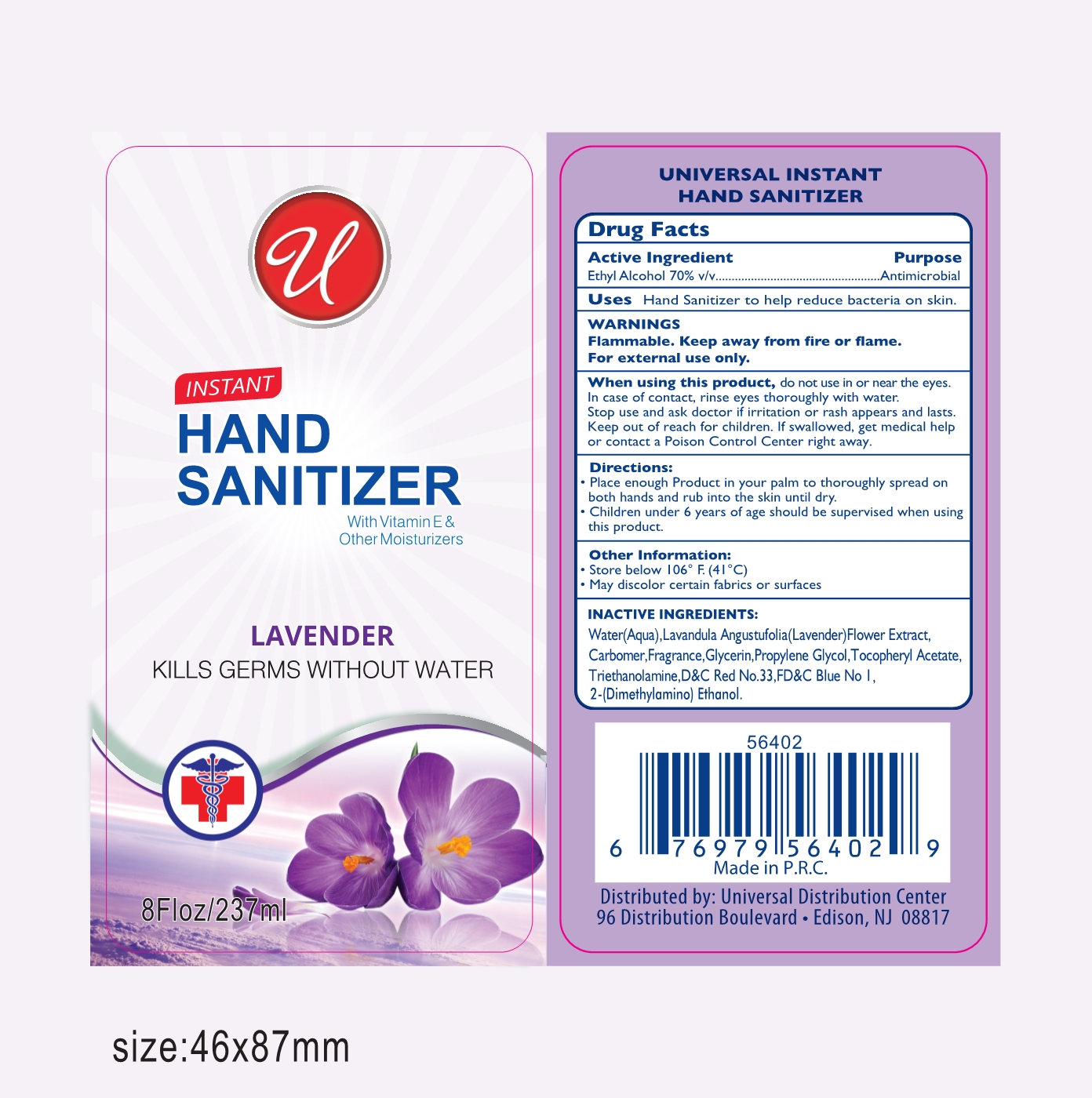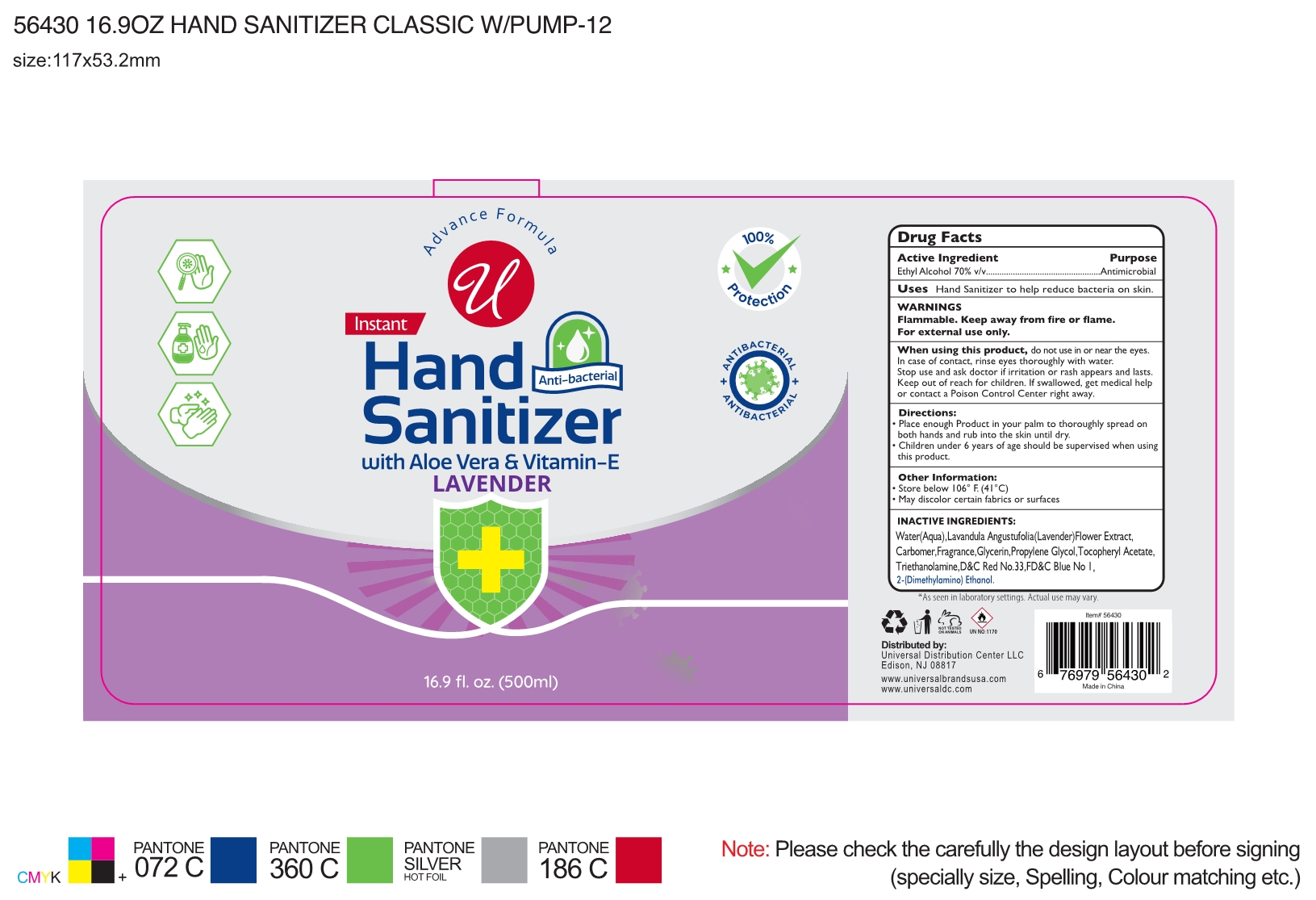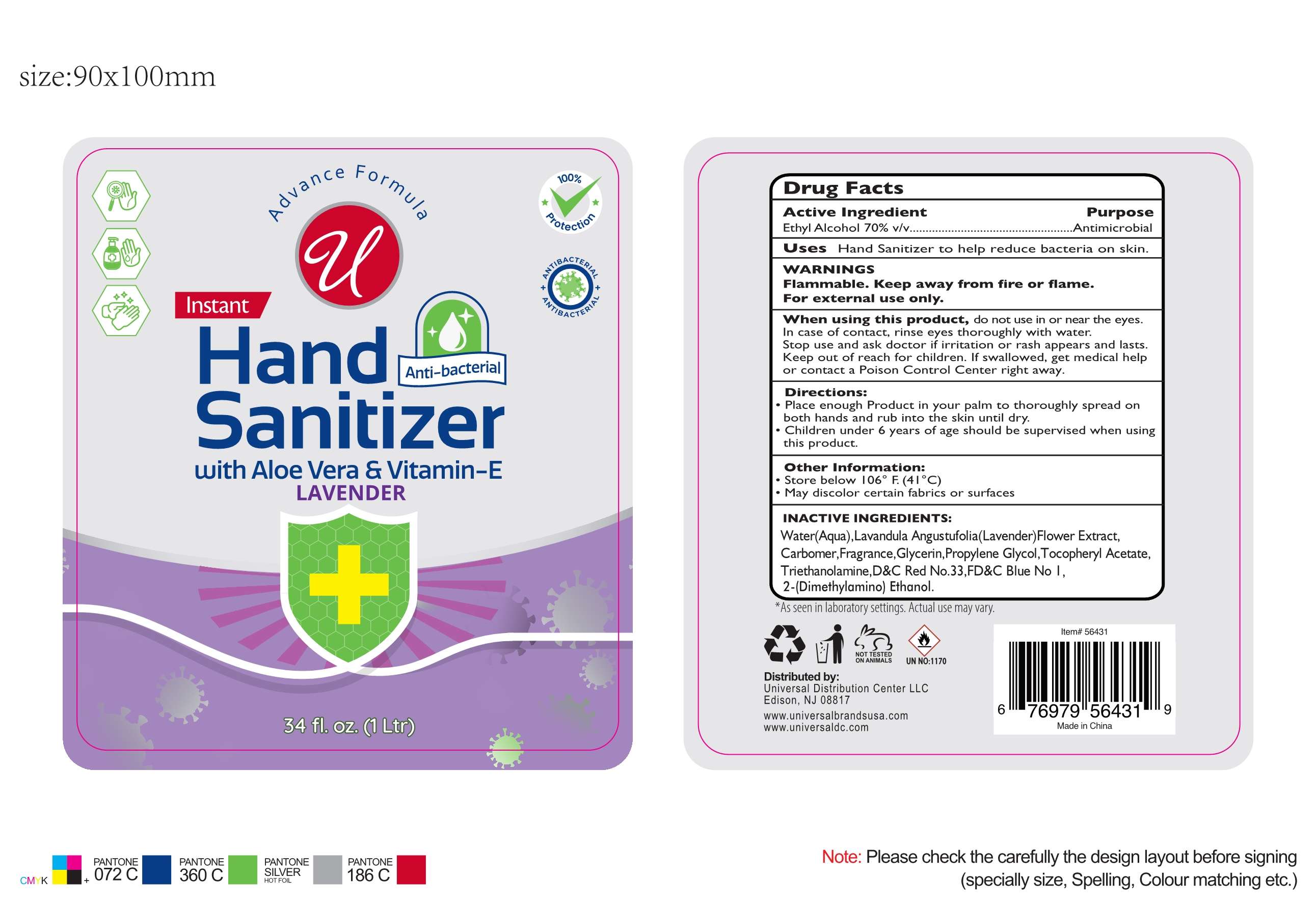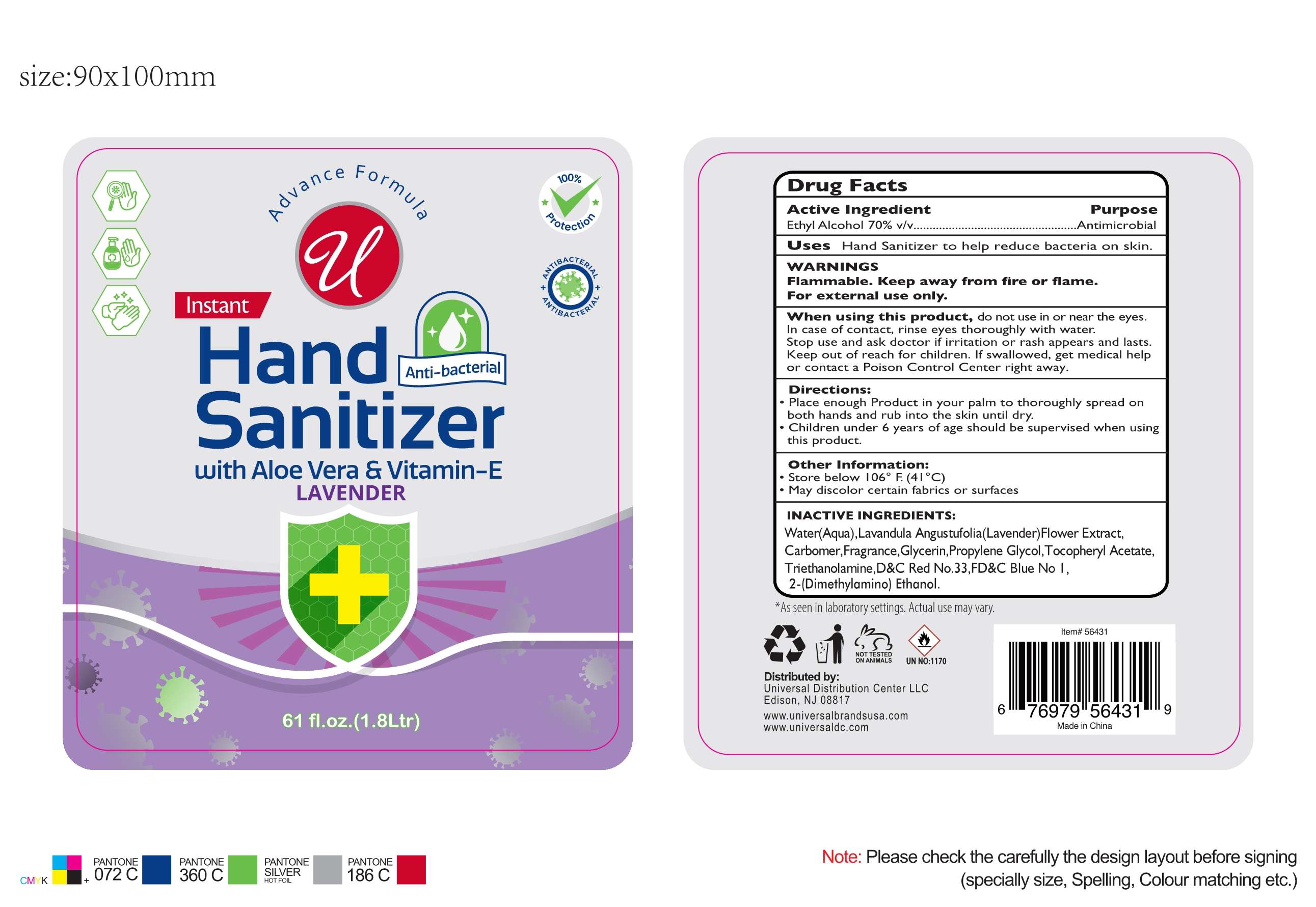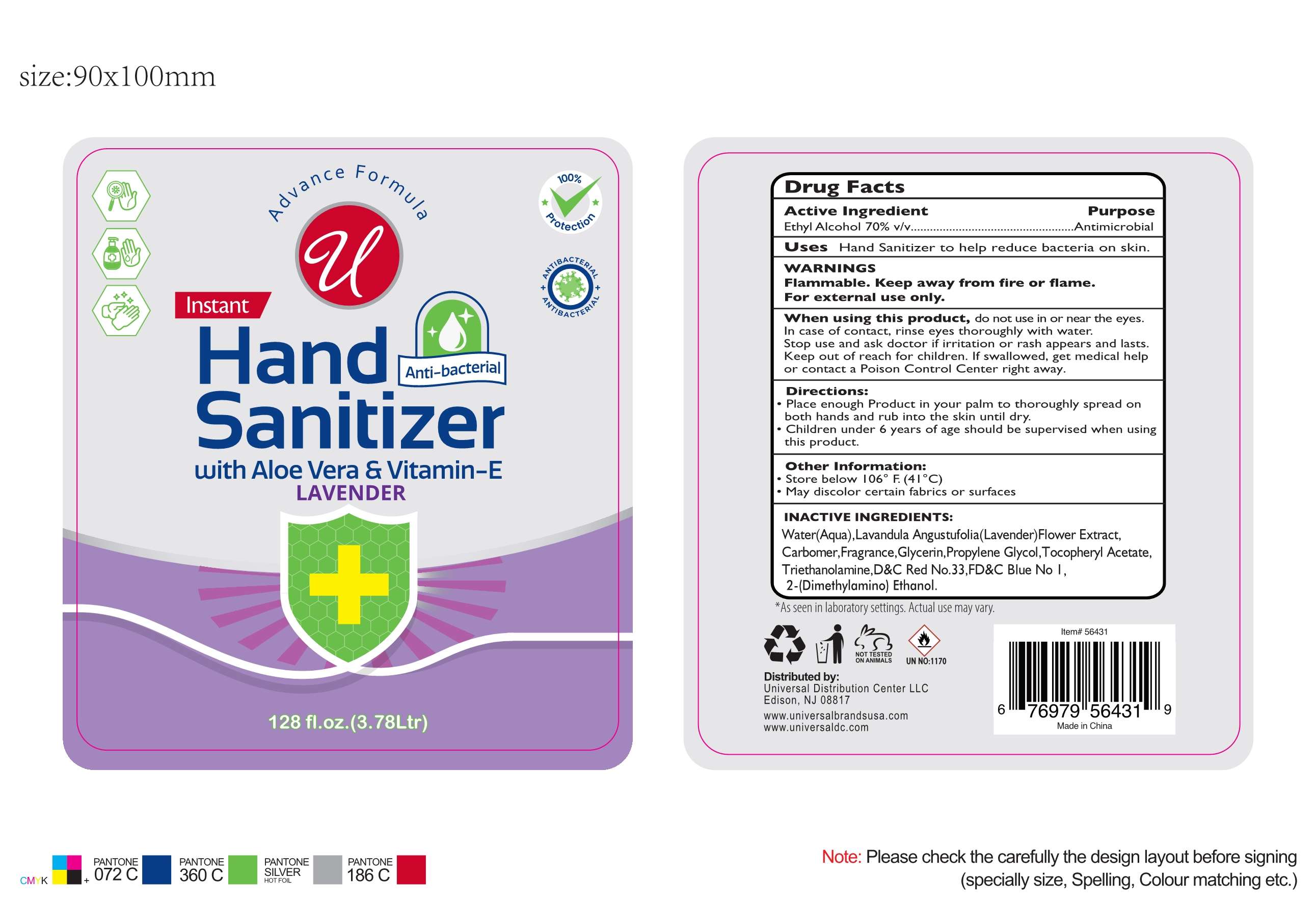 DRUG LABEL: hand sanitizer
NDC: 75701-008 | Form: LIQUID
Manufacturer: Ningbo dingchi Intelligent Manufacturing Technology Co., Ltd.
Category: otc | Type: HUMAN OTC DRUG LABEL
Date: 20210310

ACTIVE INGREDIENTS: ALCOHOL 70 mL/100 mL
INACTIVE INGREDIENTS: D&C RED NO. 33; FRAGRANCE CLEAN ORC0600327; DEANOL; LAVANDULA ANGUSTIFOLIA FLOWER; GLYCERIN; TROLAMINE; WATER; ALPHA-TOCOPHEROL ACETATE; PROPYLENE GLYCOL; CARBOMER HOMOPOLYMER, UNSPECIFIED TYPE; FD&C BLUE NO. 1

75701-008
hand sanitizer

Active Ingredient(s)

Ethyl Alcohol 70% v/v

Purpose

Antimicrobial

Use

Hand Sanitizer to help reduce bacteria on skin.

Warnings

Flammable. Keep away from fire or flame.
For external use only.

When using this product, do not use in or near the eyes.
In case of contact, rinse eyes thoroughly with water.
Stop use and ask doctor if irritation or rash appears and lasts.
Keep out of reach for children. If swallowed, get medical help or contact a

Poison Control Center right away.

do not use in or near the eyes.

When using this product, do not use in or near the eyes.

In case of contact, rinse eyes thoroughly with water.

Stop use and ask doctor if irritation or rash appears and lasts.

Keep out of reach for children. If swallowed, get medical help or contact a Poison Control Center right away.

Stop use and ask doctor if irritation or rash appears and lasts.

Keep out of reach of children.

Keep out of reach for children. If swallowed, get medical help or contact a Poison Control Center right away.

Directions

Place enough Product in your palm to thoroughly spread on both hands and rub into the skin until dry.
Children under 6 years of age should be supervised when using this product.

Other information

Store below 106°F. (41°C)
May discolor certain fabrics or surfaces

Inactive ingredients

Water(Aqua), Lavandula Angustufolia(Lavender) Flower Extract, Carbomer, Fragrance, Glycerin, Propylene Glycol, Tocopheryl Acetate, Triethanolamine,D&C Red No.33,FD&C Blue No I, 2-(Dimethylamino) Ethanol.